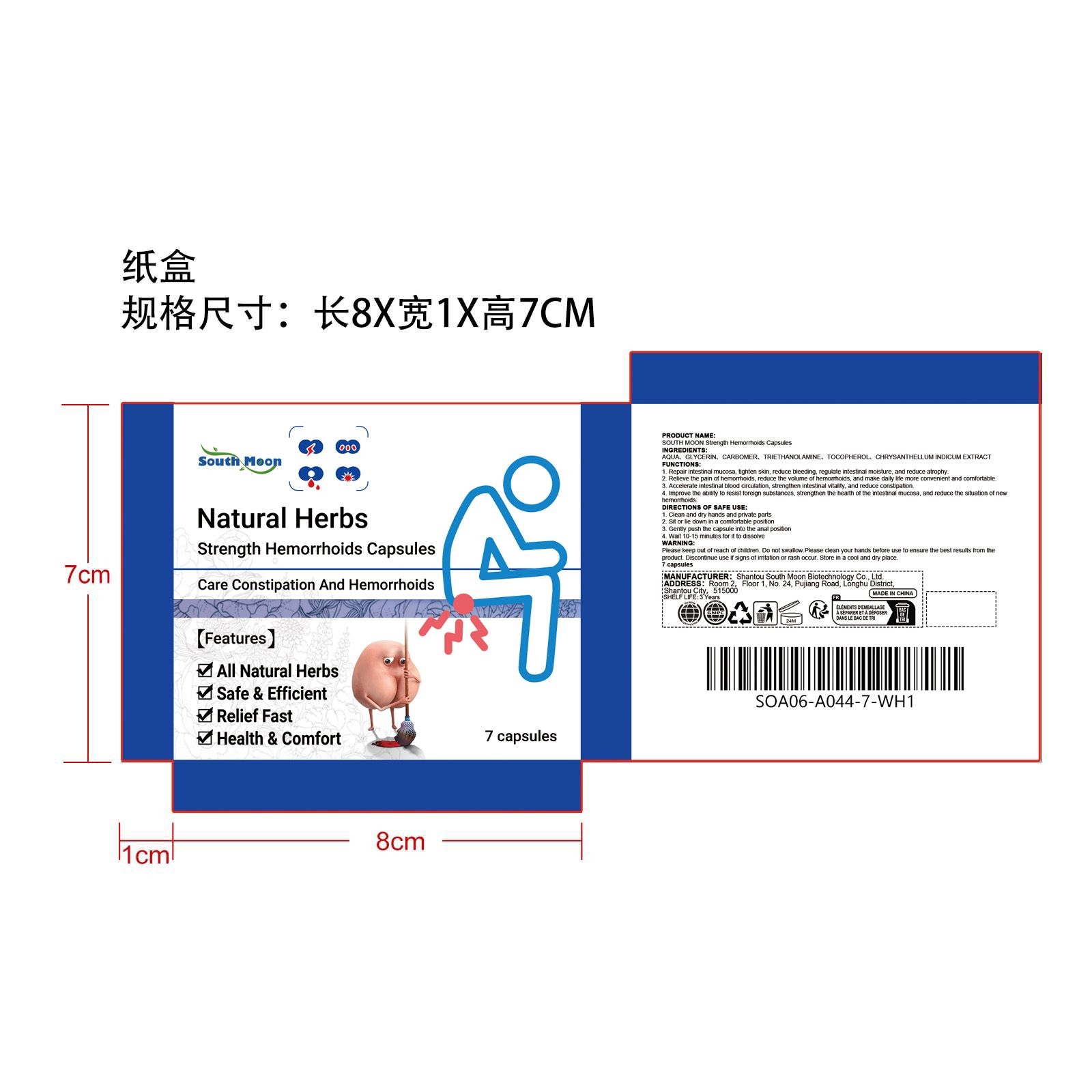 DRUG LABEL: SOUTH MOON Natural Herbs Strength Hemorrhoids
NDC: 84983-011 | Form: LIQUID
Manufacturer: Shantou South Moon Biotechnology Co., Ltd.
Category: otc | Type: HUMAN OTC DRUG LABEL
Date: 20251127

ACTIVE INGREDIENTS: CHRYSANTHELLUM INDICUM WHOLE 0.0014 mg/7 mg
INACTIVE INGREDIENTS: TRIETHANOLAMINE 0.014 mg/7 mg; CARBOMER 0.014 mg/7 mg; GLYCERIN 0.56 mg/7 mg; TOCOPHEROL 0.0014 mg/7 mg; AQUA 6.4092 mg/7 mg

INACTIVE INGREDIENT

AQUA、GLYCERIN、CARBOMER、TRIETHANOLAMINE、TOCOPHEROL

WHEN USING

1. Clean and dry hands and private parts

2. Sit or lie down in a comfortable position

3. Gently push the capsule into the anal position

4. Wait 10-15 minutes for it to dissolve

ACTIVE INGREDIENT

CHRYSANTHELLUM INDICUM WHOLE

PURPOSE

1. Repair intestinal mucosa, tighten skin, reduce bleeding, regulate intestinal moisture, and reduce atrophy.

2. Relieve the pain of hemorrhoids, reduce the volume of hemorrhoids, and make daily life more convenient and comfortable.

3. Accelerate intestinal blood circulation, strengthen intestinal vitality, and reduce constipation.

4. Improve the ability to resist foreign substances, strengthen the health of the intestinal mucosa, and reduce the situation of new hemorrhoids.

WARNINGS

Please keep out of reach of children. Do not swallow.Please clean your hands before use to ensure the best results from the product. Discontinue use if signs of irritation or rash occur. Store in a cool and dry place.

DO NOT USE

Discontinue use if signs of irritation or rash occur.

STOP USE

Discontinue use if signs of irritation or rash occur.

STORAGE AND HANDLING

Store in a cool and dry place.

KEEP OUT OF REACH OF CHILDREN

Please keep out of reach of children. Do not swallow.